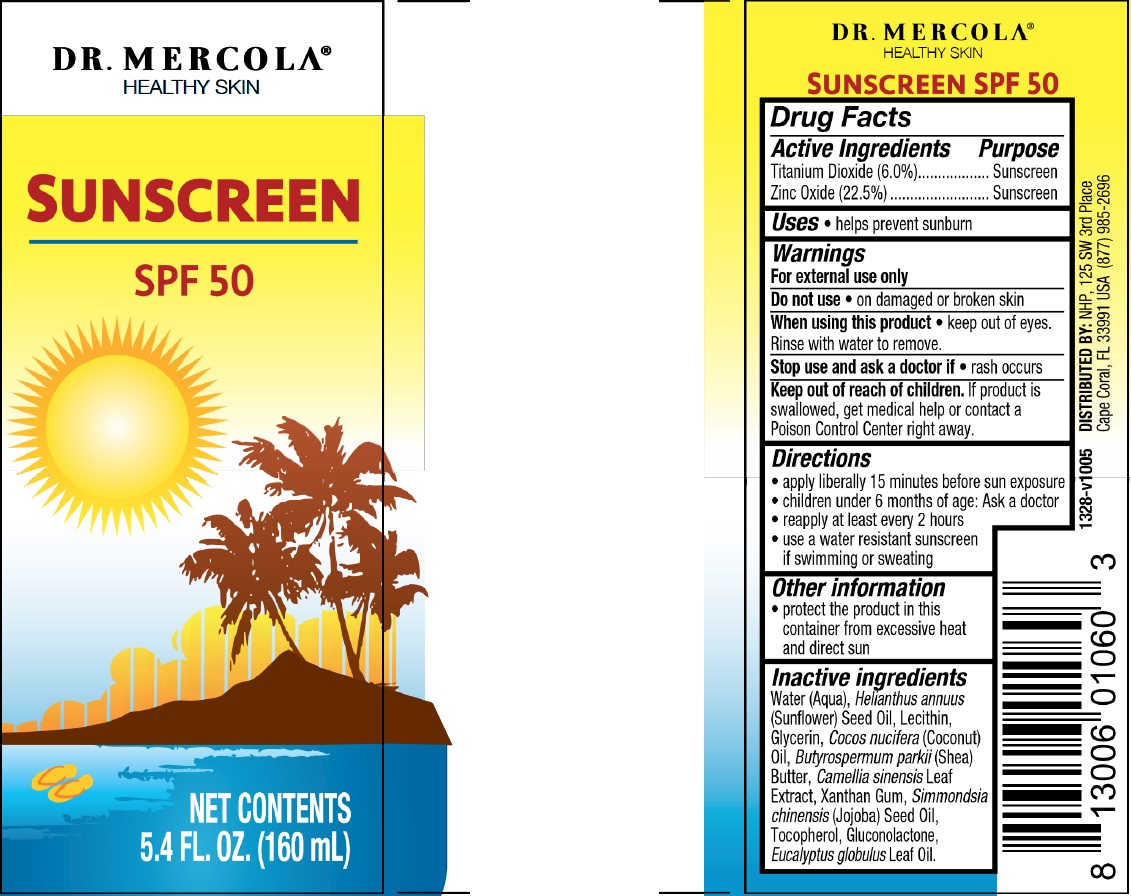 DRUG LABEL: Dr. Mercola Broad Spectrum
NDC: 71239-786 | Form: CREAM
Manufacturer: Natural Health Partners, LLC
Category: otc | Type: HUMAN OTC DRUG LABEL
Date: 20250528

ACTIVE INGREDIENTS: TITANIUM DIOXIDE 60 mg/1 mL; ZINC OXIDE 225 mg/1 mL
INACTIVE INGREDIENTS: TOCOPHEROL; GLUCONOLACTONE; WATER; HELIANTHUS ANNUUS FLOWERING TOP; GLYCERIN; COCONUT OIL; SHEA BUTTER; GREEN TEA LEAF; XANTHAN GUM; JOJOBA OIL; EUCALYPTUS OIL

Dr. Mercola Broad Spectrum SPF-50 Cream

Active Ingredients

Titanium Dioxide (6.0%)

Zinc Oxide (22.5%)

Purpose

Sunscreen

Uses

- helps prevent sunburn

Warnings

For external use only

Do not use

- on damaged or broken skin

When using this product

- keep out of eyes. Rinse with water to remove.

Stop use and ask a doctor if

- rash occurs

Keep out of reach of children.

If product is swallowed, get medical help or contact a Poison Control Center right away.

Directions

- apply liberally 15 minutes before sun exposure
- children under 6 months of age: Ask a doctor
- reapply at least every 2 hours
- use a water resistant sunscreen if swimming or sweating

Other information

- protect the product in this container from excessive heat and direct sun

Inactive ingredients

Water (Aqua), Helianthus annuus (Sunflower) Seed Oil, Lecithin, Glycerin, Cocos nucifera (Coconut) Oil, Butyrospermum parkii (Shea) Butter, Camellia sinensis Leaf Extract, Xanthan Gum, Simmondsia chinensis (Jojoba) Seed Oil, Tocopherol, Gluconolactone, Eucalyptus globulus Leaf Oil.